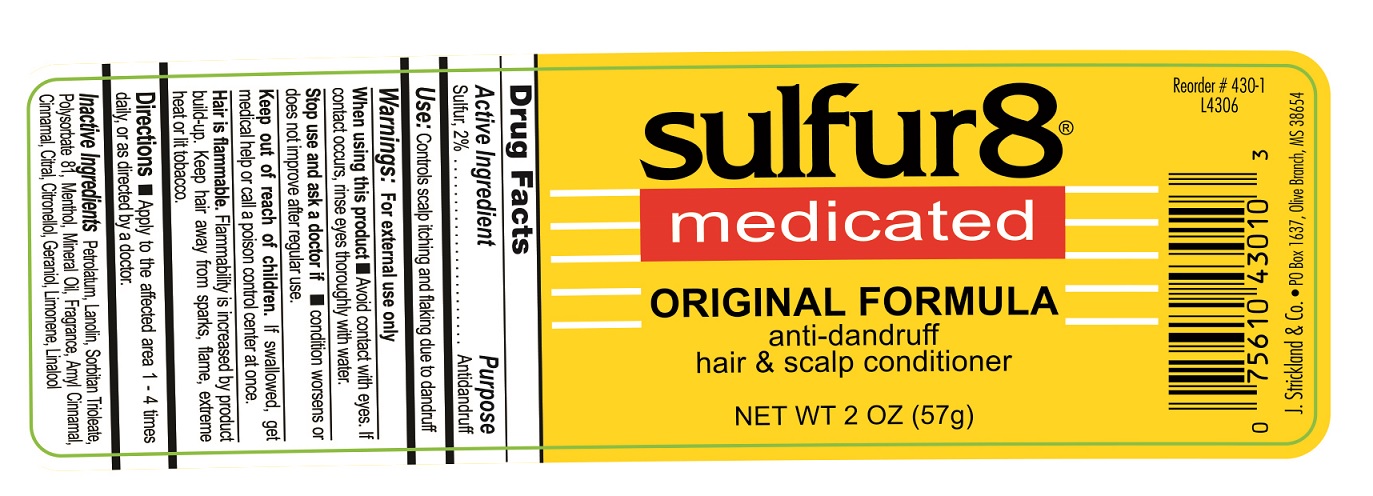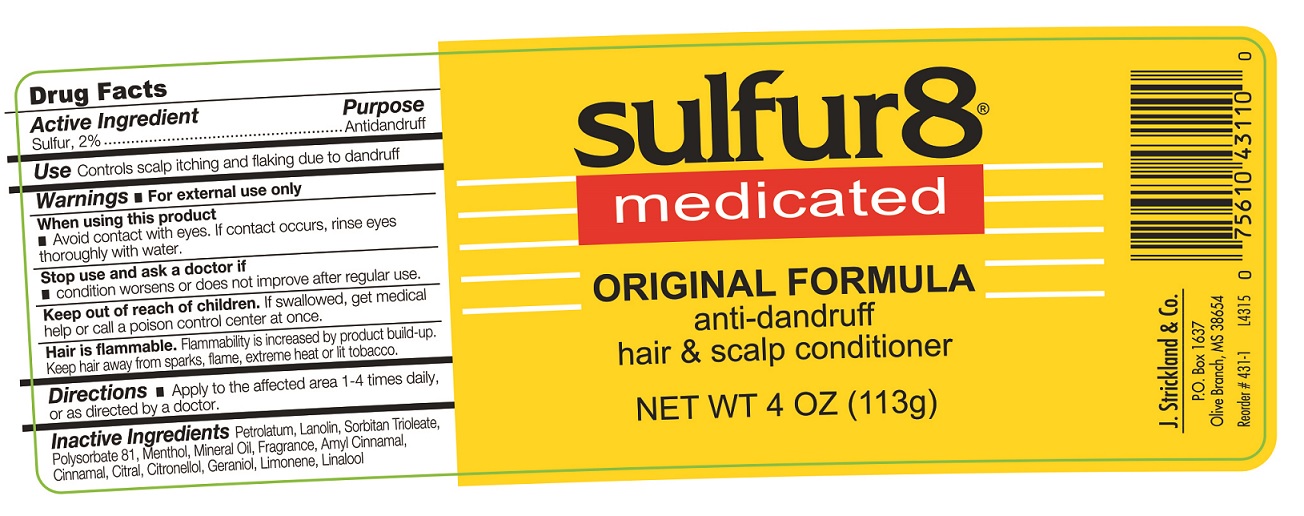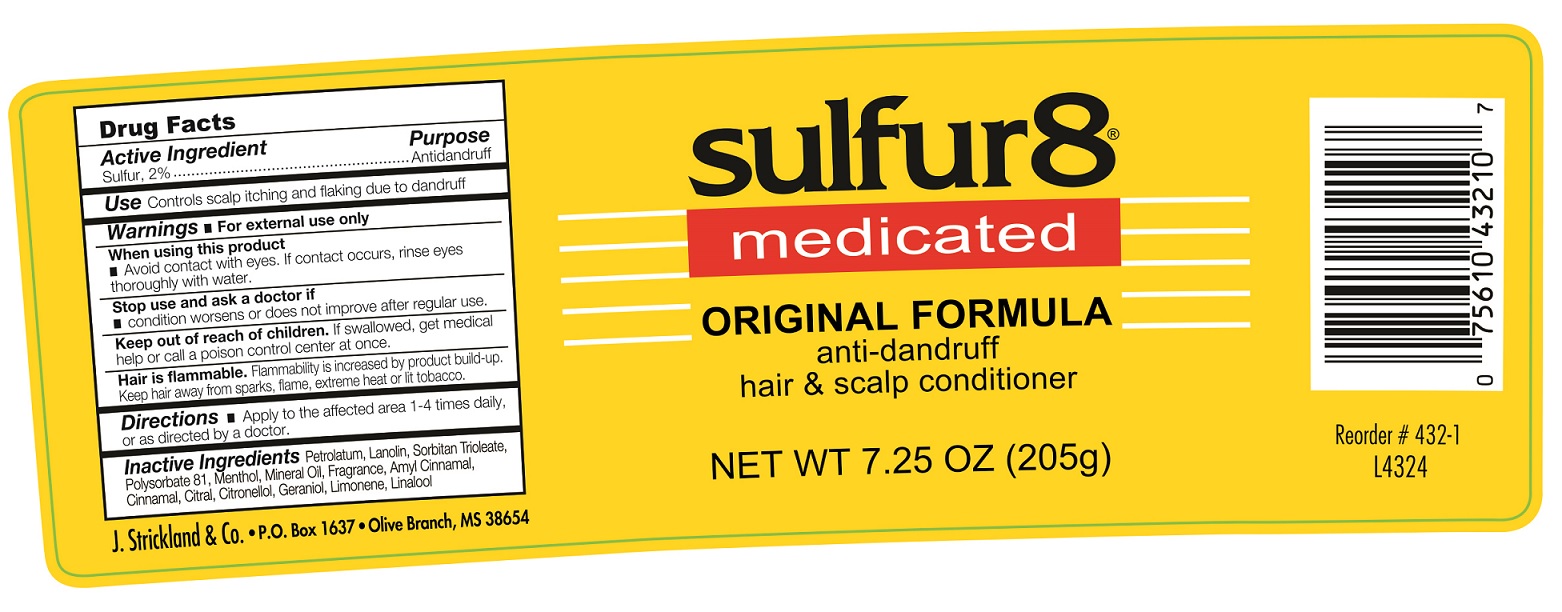 DRUG LABEL: Sulfur 8 Original Anti-Dandruff Hair and Scalp Conditioner
NDC: 12022-017 | Form: OINTMENT
Manufacturer: J. Strickland & Co.
Category: otc | Type: HUMAN OTC DRUG LABEL
Date: 20231021

ACTIVE INGREDIENTS: SULFUR 20 mg/1 g
INACTIVE INGREDIENTS: PETROLATUM; LANOLIN; SORBITAN TRIOLEATE; MENTHOL; MINERAL OIL; .ALPHA.-AMYLCINNAMALDEHYDE; CINNAMALDEHYDE; CITRAL; .BETA.-CITRONELLOL, (R)-; GERANIOL; LIMONENE, (+)-; LINALOOL, (+/-)-

Sulfur 8 Original Anti-Dandruff Hair and Scalp Conditioner

Active Ingredient

Sulfur, 2%

Purpose

Antidandruff

Use:

Controls scalp itching and flaking due to dandruff

Warnings:

For external use only

When using this product

- Avoid contact with eyes. If contact occurs, rinse eyes throughly with water.

Stop use and ask a doctor if

- condition worsens or does not improve after regular use.

Keep out of reach of children

If swallower, get medical help or call a poison control center at once.

Directions

- Apply to the affected area 1-4 times daily, or as directed by a doctor.

Inactive Ingredients

Petrolatum, Landin, Sorbitan Trioleate, Pclysorbate 81, Menthol, Mineral Oil, Fragrance, Amyl Cinnamal, Cinnamal, Citral, Citronellol, Geraniol, Limonene, Linalool